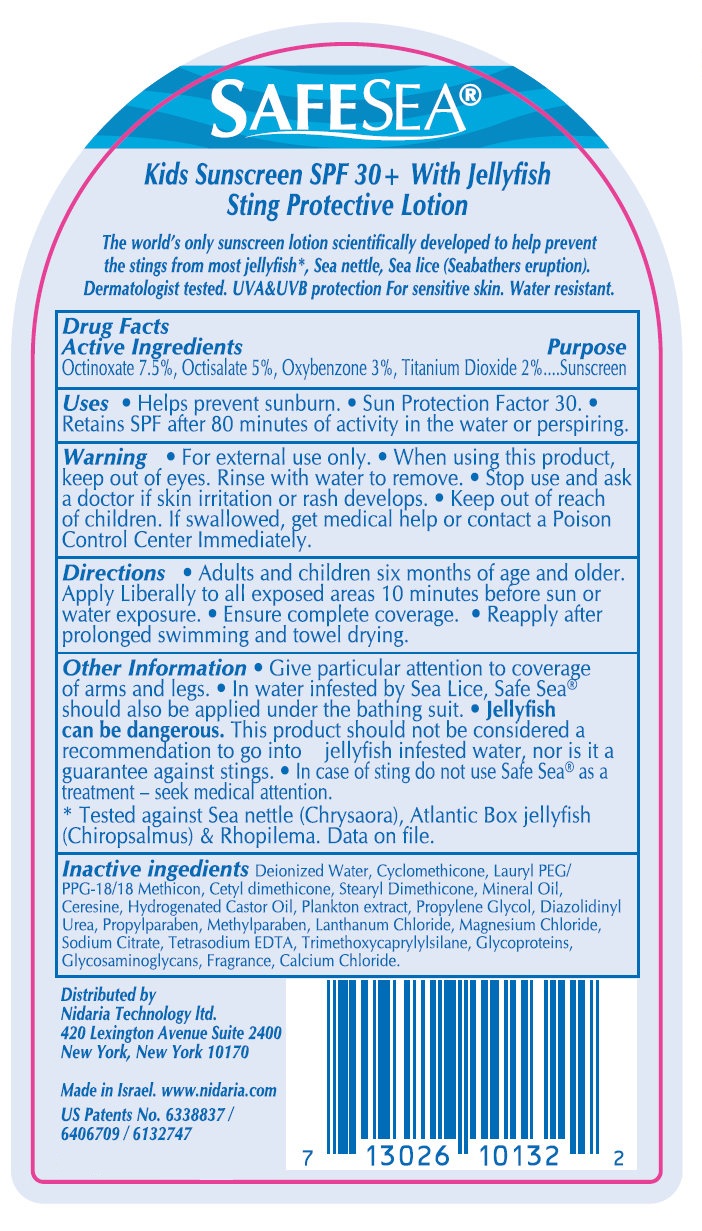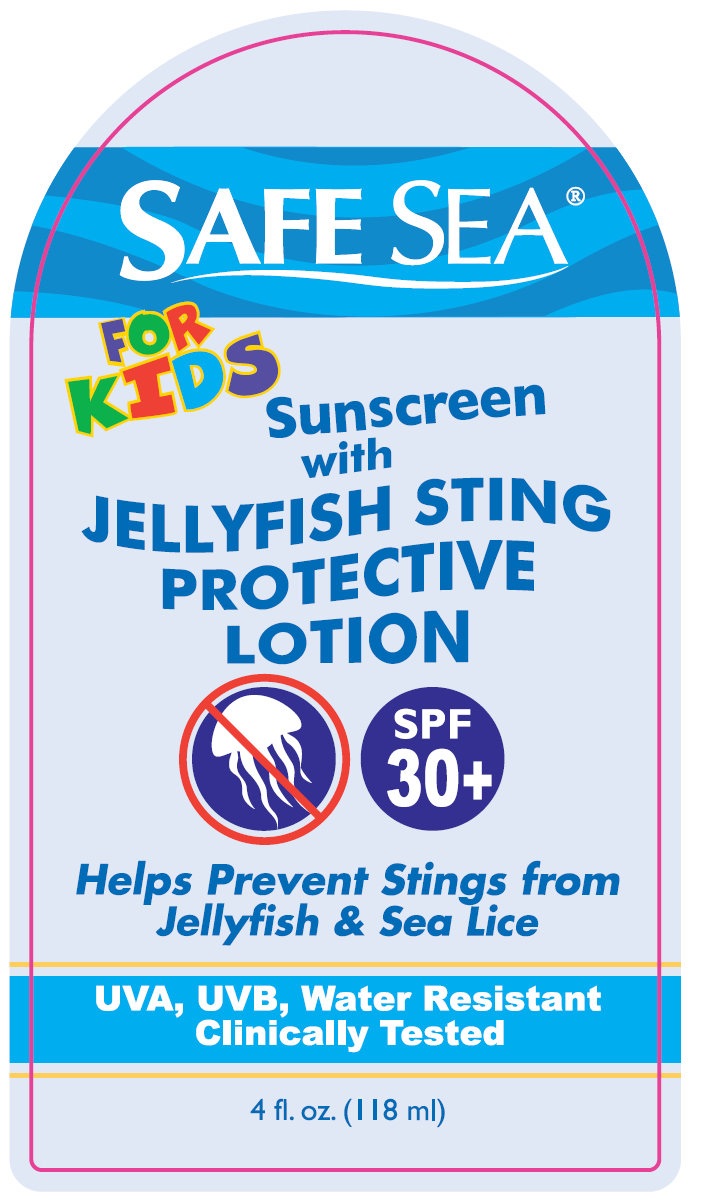 DRUG LABEL: Safe Sea For Kids Sunscreen With Jellyfish Sting Protective SPF 30 Plus
NDC: 65435-0133 | Form: LOTION
Manufacturer: Nidaria Technology Ltd.
Category: otc | Type: HUMAN OTC DRUG LABEL
Date: 20111121

ACTIVE INGREDIENTS: OCTINOXATE 7.5 mL/100 mL; OCTISALATE 5 mL/100 mL; OXYBENZONE 3 mL/100 mL; TITANIUM DIOXIDE 2 mL/100 mL
INACTIVE INGREDIENTS: WATER; CYCLOMETHICONE; MINERAL OIL; SODIUM DICHLOROACETATE; HYDROGENATED CASTOR OIL; PROPYLENE GLYCOL; DIAZOLIDINYL UREA; PROPYLPARABEN; METHYLPARABEN; MAGNESIUM CHLORIDE; SODIUM CITRATE; EDETATE SODIUM; TRIMETHOXYCAPRYLYLSILANE; CALCIUM CHLORIDE

Safe Sea For Kids Sunscreen With Jellyfish Sting Protective SPF 30 Plus

Active Ingredients

Active Ingredients Purpose
Octinoxate 7.5 %, Octisalate 5 %, Oxybenzone 3 %, Titanium Dioxide 2 %....Sunscreen

Uses

- Helps prevent sunburn. - Sun Protection Factor 30. - Retains SPF after 80 minutes of activity in the water or perspiring.

Warning

- For external use only.

When using this product

keep out of eyes. Rinse with water to remove.

Stop use and ask a doctor

if skin irritation or rash develops.

Keep out of reach of children. If swallowed, get medical help or contact a Poison Control Center Immediately.

Directions

- Adults and children six months of age and older. Apply Liberally to all exposed areas 10 minutes before sun or water exposure. - Ensure complete coverage. - Reapply after prolonged swimmimg and towel drying.

Other Information

- Give particular attention to coverage of arms and legs. - In water infested by Sea Lice, Safe Sea should also be applied under the bathing suit. Jellyfish can be dangerous. This product should not be considered a recommendation to go into jellyfish infested water, nor is it a guarantee against stings. - In case of sting do not use Safe Sea as a treatment - seek medical attention. * Tested against Sea nettle (Chrysaora), Atlantic Box jellyfish (Chiropsalmus) and Rhopilema. Date on file.

Inactive ingredients

Deionized Water, Cyclomethicone, Lauryl PEG/PPG-18/18 Methicon, Cetyl dimethicone, Stearyl Dimethicone, Mineral Oil, Ceresine, Hydrogenated Castor Oil, Plankton extract, Propylene Glycol, Diazolidinyl Urea, Propylparaben, Methylparaben, Lanthanum Chloride, Magnesium Chloride, Sodium Citrate, Tetrasodium EDTA, Trimethoxycaprylylsilane, Glycoproteins, Glycosaminoglycans, Fragrance, Calcium Chloride.

Purpose

Sunscreen

Description

SAFE SEA Kids Sunscreen SPF 30+ With Jellyfish Sting Protective Lotion The world's only sunscreen lotion scientifically developed to help prevent the stings from most jellyfish*, Sea nettle, Sea lice (Seabathers eruption). Dermatologist tested. UVAandUVB protection For sensitive skin. Water resistant. Distributed by Nidaria Technology ltd. 420 Lexington Avenue Suite 2400 New York, New York 10170 Made in Israel. www.nidaria.com US Patents No. 6338837 / 6406709 / 6132747 NDC - 0654350131 7 13026 10132 2

PACKAGE LABEL

SAFE SEA Kids Sunscreen SPF 30+ With Jellyfish Sting Protective Lotion

PACKAGE LABEL

SAFE SEA FOR KIDS Sunscreen with JELLYFISH STING PROTECTIVE LOTION SPF 30+ Helps Prevent Stings from Jellyfish and Sea Lice UVA, UVB, Water Resistant Clinically Tested 4 fl. oz. (118 ml)